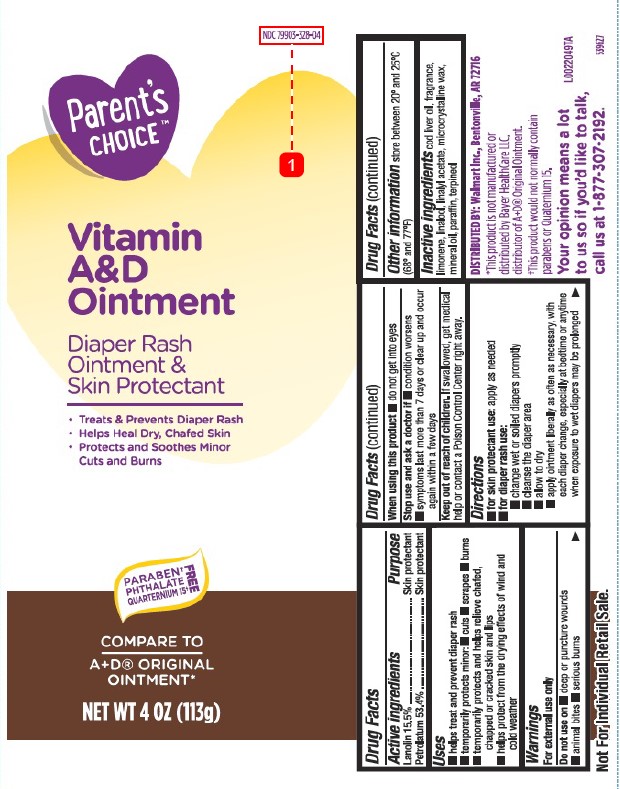 DRUG LABEL: Vitamin A D
NDC: 79903-328 | Form: OINTMENT
Manufacturer: Walmart Inc.
Category: otc | Type: HUMAN OTC DRUG LABEL
Date: 20260227

ACTIVE INGREDIENTS: PETROLATUM 534 mg/1 g; LANOLIN 155 mg/1 g
INACTIVE INGREDIENTS: COD LIVER OIL; LIMONENE, (+)-; LINALOOL, (+/-)-; LINALYL ACETATE; MICROCRYSTALLINE WAX; MINERAL OIL; PARAFFIN; TERPINEOL

Parents Choice 013.001/013AC
Vitamin A & D Ointment

ACTIVE INGREDIENTS

Lanolin 15.5%

Petrolatum 53.4%

PURPOSE

Skin protectant

Uses

- helps treat and prevent diaper rash
- temporarily protects minor: ■ cuts ■ scrapes ■ burns
- temporarily protects and helps relieve chafed, chapped or cracked skin and lips
- helps protect from the drying effects of wind and cold weather

Warnings

For external use only

Do not use on

- deep or puncture wounds
- animal bites
- serious burns

When using this product

- do not get into eyes

Stop use and ask a doctor if

- condition worsens
- symptoms last more than 7 days or clear up and occur again within a few days

Keep out of reach of children.

If swallowed, get medical help or contact a Poison Control Center right away.

Directions

- for skin protectant use:apply as needed
- for diaper rash use:
  ■ change wet or soiled diapers promptly
  ■ cleanse the diaper area
  ■ allow to dry
  ■ apply ointment liberally as often as necessary, with each diaper change, especially at bedtime or anytime when exposure to wet diapers may be prolonged

Other information

store between 20º and 25ºC (68º and 77º F)

INACTIVE INGREDIENTS

cod liver oil, fragrance, limonene, linalool, linalyl acetate, microcrystalline wax, mineral oil, paraffin, terpineol

Disclaimer

*This product is not manufactured or distributed by Bayer HealthCare LLC, distributor of A+D®Original Ointment.

†This product would not normally contain parabens or Quaternium 15.

ADVERSE REACTION

DISTRIBUTED BY: Walmart Inc., Bentonville, AR 72716

Your opinion means a lot to us so if you'd like to talk, call us at 1-877-307-2192.

PRINCIPAL DISPLAY PANEL

NDC 79903-328-04

Parent's CHOICE™

Vitamin

A&D

Ointment

Diaper Rash

Ointment &

Skin Protectant

- Treats & Prevents Diaper Rash
- Helps Heal Dry, Chafed Skin
- Protects and Soothes Minor Cuts and Burns

FREE

PARABEN†

PHTHALATE

QUARTERIUM 15†

COMPARE TO A + D ORIGINAL OINTMENT*

NET WT 4 OZ (113g)